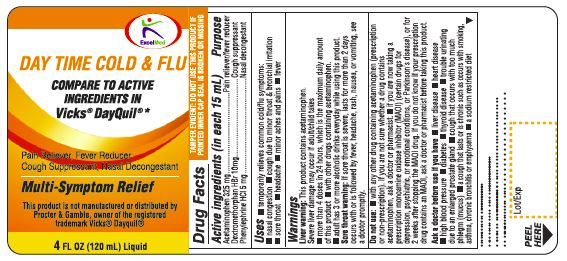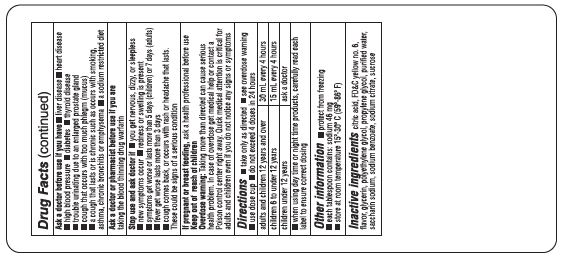 DRUG LABEL: Daytime Cough
NDC: 71027-040 | Form: LIQUID
Manufacturer: KINGSTON PHARMA LLC
Category: otc | Type: HUMAN OTC DRUG LABEL
Date: 20190130

ACTIVE INGREDIENTS: ACETAMINOPHEN 325 mg/15 mL; DEXTROMETHORPHAN HYDROBROMIDE 10 mg/15 mL; PHENYLEPHRINE HYDROCHLORIDE 5 mg/15 mL
INACTIVE INGREDIENTS: BUTYLATED HYDROXYANISOLE; EDETATE DISODIUM; FD&C YELLOW NO. 6; METHYL SALICYLATE; GLYCERIN; MENTHOL, UNSPECIFIED FORM; SODIUM PHOSPHATE, MONOBASIC, UNSPECIFIED FORM; POLYETHYLENE GLYCOL, UNSPECIFIED; PROPYLENE GLYCOL; SACCHARIN SODIUM; SUCROSE; XANTHAN GUM; WATER

Daytime Cough

Active Ingredient (in each 15 mL = 1 tablespoon):
Acetaminophen 325 mg
Dextromethorphan HBr 10 mg
Phenylephrine HCl 5 mg

Purpose: Pain reliever/fever reducer
Cough suppressant
Nasal decongestant

Uses

- Temporarily relieves these common cold/flu symptoms
  1. Minor aches and pains
  2. Headache
  3. Sore throat
  4. Nasal congestion
  5. Fever
  6. Cough due to minor throat and bronchial irritation

Warnings
Liver warning: This product contains acetaminophen. Severe liver damage may occur if adult/child takes

- More than 4 doses in 24 hours, which is the maximum daily amount for this product.
- With other drugs containing acetaminophen.
- Adult has 3 or more alcoholic drinks every day while using this product.

Sore throat warning: If sore throat is severe, persists for more than 2 days, is accompanied or followed by fever, headache, rash, nausea, or vomiting, consult a doctor promptly.

Do not use:

- With any other drug containing acetaminophen (prescription or nonprescription). If you are not sure whether a drug contains acetaminophen, ask a doctor or pharmacist.
- If you are now taking a prescription monoamine oxidase inhibitor (MAOI) (certain drugs for depression, psychiatric, or emotional conditions or parkinson’s disease), or for 2 weeks after stopping the MAOI drug. If you do not know if your prescription drug contains an MAOI, ask a doctor or pharmacist before taking this product.
- If you have ever had an allergic reaction to this product or any of its ingredients.

TAMPER EVIDENT: DO NOT USE IF PRINTED SAFETY SEAL ON THE BOTTLE IS BROKEN OR MISSING.

Ask a doctor before use if you have

- Liver disease
- Heart disease
- High blood pressure
- Thyroid disease
- Diabetes
- Trouble urinating due to an enlarged prostate gland
- Persistent or chronic cough such as occurs with smoking, asthma or emphysema
- Cough that occurs with too much phlegm (mucus)
- A sodium restricted diet

Ask a doctor or pharmacist before use if you are

- Taking the blood thinning drug warfarin

When using this product

- Do not exceed recommended dosage (see overdose warning)

Stop use and ask doctor if

- Nervousness, dizziness or sleeplessness occur
- Symptoms get worse or last more than 5 days (children) or 7 days (adults)
- Fever gets worse or lasts more than 3 days
- Redness or swelling is present
- New symptoms occur
- Cough comes back or occurs with rash or headache that lasts

These could be signs of a serious condition

KEEP OUT OF REACH OF CHILDREN

Keep this and all drugs out of the reach of children.
Overdose Warning: In case of accidental overdose, seek professional assistance or contact a Poison control center right away. Quick medical attention is critical for adults as well as children even if you do not notice any signs or symptoms.

PREGNANCY OR BREAST FEEDING

If pregnant or breast-feeding, ask a health professional before use.

Directions:

- Do not take more than directed. (see overdose warning)
- Use enclosed dosing cup.
- Do not take more than 4 doses in 24-hours.
- Adults and children 12 years and over: take 2 tablespoons (TBSP) or 30 mL every 4 hours.
- Children 6 to under 12 years: take 1 tablespoon (TBSP) or 15 mL every 4 hours.
- Children 4 to under 6 years: ask a doctor
- Children under 4 years: do not use
- When using other Daytime or Nite time products, carefully read each label to insure correct dosing

Other information

- Store between 20-25 degree Celsius (68-77 degree Fahrenheit)
- Each tablespoon contains: Sodium 50mg

INACTIVE INGREDIENT

Inactive ingredients: Butylated hydroxyanisole, Edetate disodium, FD&C yellow 6, flavor, Glycerin, Menthol, Monobasic sodium phosphate, Polyethylene glycol, Propylene glycol, Saccharin sodium, Sucrose, Xanthan gum and Purified Water.

HOW SUPPLIED

(packs: 4oz) Kingston NDC# 71027-040-06
Manufactured by: Kingston Pharma LLC
5 County Route 42
Massena, NY 13662